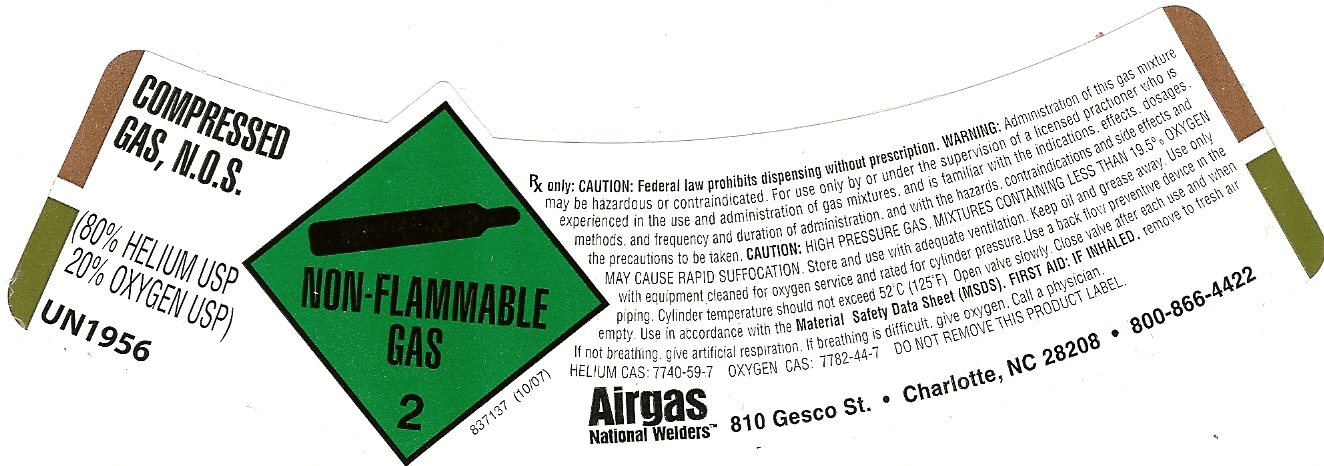 DRUG LABEL: Helium Oxygen
NDC: 11896-0017 | Form: GAS
Manufacturer: Airgas National Welders
Category: prescription | Type: HUMAN PRESCRIPTION DRUG LABEL
Date: 20101020

ACTIVE INGREDIENTS: Helium 800 mL/1 L; Oxygen 200 min/1 L

HELIUM OXYGEN LABEL 80 20

PACKAGE LABEL

COMPRESSED GAS,N.O.S. (80% HELIUM USP,20% OXYGEN USP)UN1956 NON-FLAMMABLE GAS 2 837137 (10/07) RX ONLY:CAUTION:FEDERAL LAW PROHIBITS DISPENSING WITHOUT PRESCRIPTION.WARNING:ADMINISTRATION OF THIS GAS MIXTURE MAY BE HAZARDOUS OR CONTRAINDICATED.FOR USE ONLY BY OR UNDER THE SUPERVISION OF A LICENSED PRACTITIONER WHO IS EXPERIENCED IN THE USE AND ADMINISTRATION OF GAS MIXTURES, AND IS FAMILIAR WITH THE INDICATIONS , EFFECTS, DOSAGES, METHODS, AND FREQUENCY AND DURATION OF ADMINISTRATION, AND WITH THE HAZARDS, CONTRAINDICATIONS AND SIDE EFFECTS AND THE PRECAUTIONS TO BE TAKEN.CAUTION:HIGH PRESSURE GAS. MIXTURES CONTAINING LESS THAN 19.5% OXYGEN MAY CAUSE RAPID SUFFOCATION. STORE AND USE WITH ADEQUATE VENTILATION. KEEP OIL AND GREASE AWAY. USE ONLY WITH EQUIPMENT CLEANED FOR OXYGEN SERVICE AND RATED FOR CYLINDER PRESSURE. USE A BACK FLOW PREVENTIVE DEVICE IN THE PIPING. CYLINDER TEMPERATURE SHOULD NOT EXCEED 52'C (125'F). OPEN VALVE SLOWLY. CLOSE VALVE AFTER EACH USE AND WHEN EMPTY. USE IN ACCORDANCE WITH MATERIAL SAFETY DATA SHEET (MSDS). FIRST AID: IF INHALED, REMOVE TO FRESH AIR. IF NOT BREATHING GIVE ARTIFICIAL RESPIRATION. IF BREATHING IS DIFFICULT, GIVE OXYGEN. CALL A PHYSICIAN. HELIUM CAS:7440-59-7 OXYGEN CAS:7782-44-7 DO NOT REMOVE THIS LABEL. AIRGAS NATIONAL WELDERS 810 GESCO ST.* CHARLOTTE, NC 28208* 800-866-4422